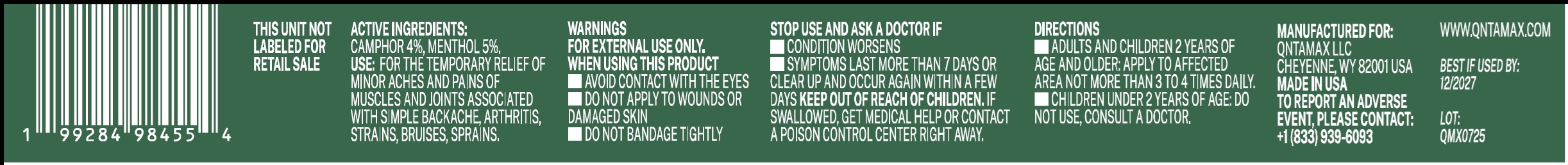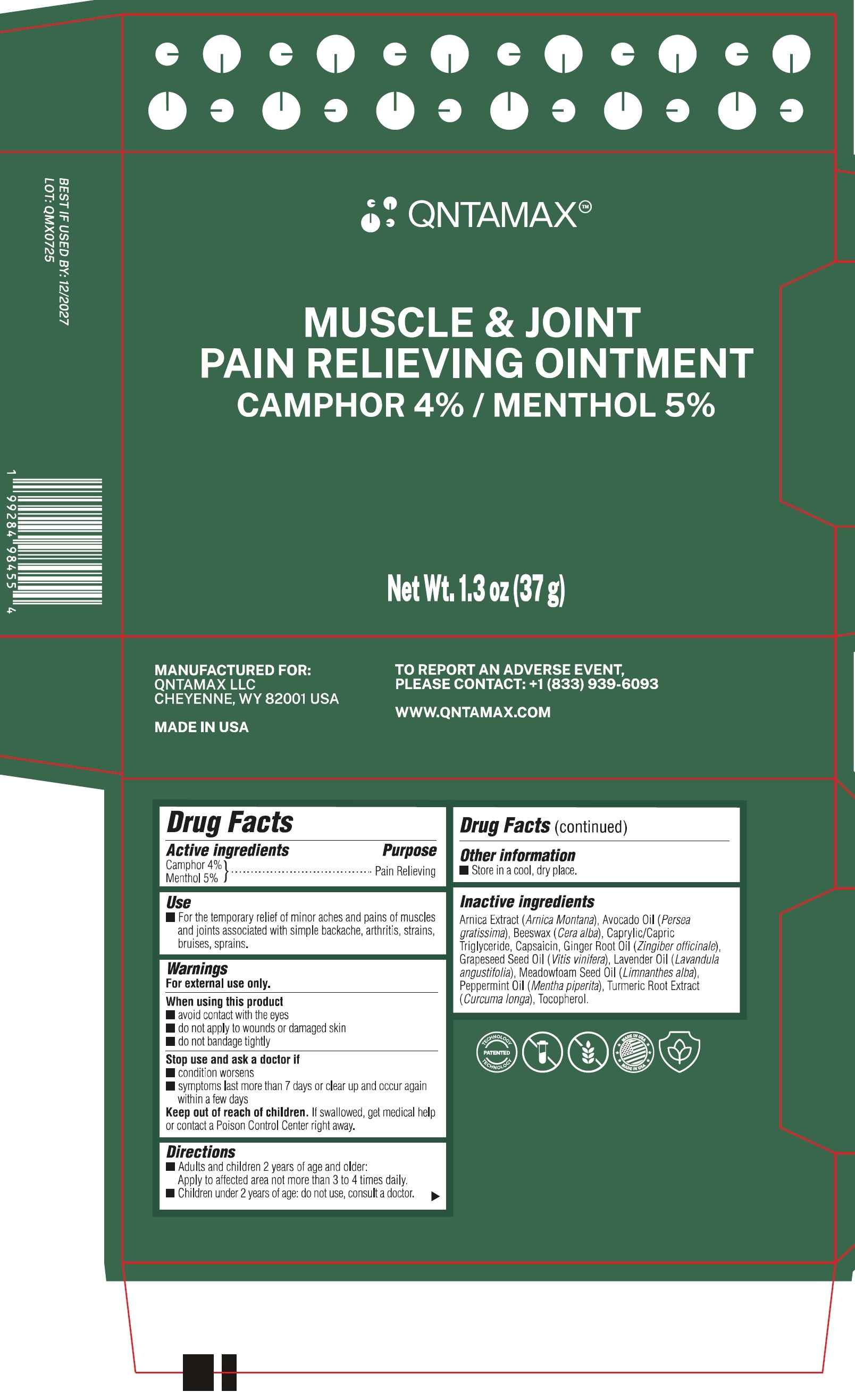 DRUG LABEL: QNTAMAX Muscle and Joint Pain Relieving
NDC: 85892-000 | Form: OINTMENT
Manufacturer: Qntamax LLC
Category: otc | Type: HUMAN OTC DRUG LABEL
Date: 20260106

ACTIVE INGREDIENTS: CAMPHOR (SYNTHETIC) 40 mg/1 g; MENTHOL 50 mg/1 g
INACTIVE INGREDIENTS: ARNICA MONTANA WHOLE; AVOCADO OIL; YELLOW WAX; MEDIUM-CHAIN TRIGLYCERIDES; CAPSAICIN; GINGER OIL; LAVENDER OIL; MEADOWFOAM SEED OIL; PEPPERMINT OIL; TURMERIC; TOCOPHEROL

QNTAMAX Muscle & Joint Pain Relieving Ointment

Active ingredients

Camphor 4%
Menthol 5%

Purpose

Pain Relieving

Use

- For the temporary relief of minor aches and pains of muscles and joints associated with simple backache, arthritis, strains, bruises, sprains.

Warnings

For external use only.

When using this product

- avoid contact with the eyes
- do not apply to wounds or damaged skin
- do not bandage tightly

Stop use and ask a doctor if

- condition worsens
- symptoms last more than 7 days or clear up and occur again within a few days

Keep out of reach of children.

If swallowed, get medical help or contact a Poison Control Center right away.

Directions

- Adults and children 2 years of age and older: Apply to affected area not more than 3 to 4 times daily.
- Children under 2 years of age: do not use, consult a doctor.

Other information

- Store in a cool, dry place.

Inactive ingredients

Arnica Extract (Arnica Montana), Avocado Oil (Persea gratissima), Beeswax (Cera alba), Caprylic/Capric Triglyceride, Capsaicin, Ginger Root Oil (Zingiber officinale), Grapeseed Seed Oil (Vitis vinifera), Lavender Oil (Lavandula angustifolia), Meadowfoam Seed Oil (Limnanthes alba), Peppermint Oil (Mentha piperita), Turmeric Root Extract (Curcuma longa), Tocopherol.